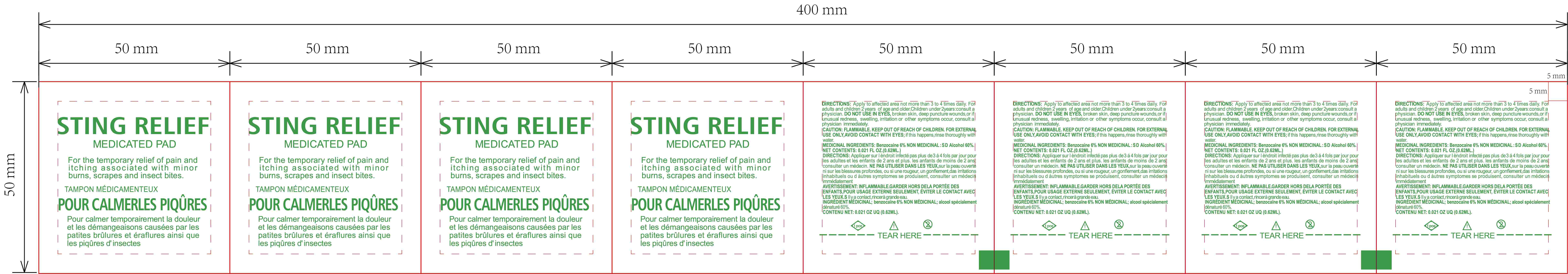 DRUG LABEL: Sting Relief prep Pad
NDC: 84449-003 | Form: PATCH
Manufacturer: SHENZHEN BENLIJU BIO-TECH CO.,LTD
Category: otc | Type: HUMAN OTC DRUG LABEL
Date: 20260105

ACTIVE INGREDIENTS: GLYCERIN 10 mg/1 g; LANOLIN 10 mg/1 g; CITRONELLA OIL 10 mg/1 g; BENZOCAINE 60 mg/1 g; ALOE 10 mg/1 g
INACTIVE INGREDIENTS: WATER

ACTIVE INGREDIENT

Aloevera，Glycerin，Lanolin，Citronellaoil，Benzocaine

PURPOSE

disinfect

INDICATIONS AND USAGE

Mainly used for wiping before mosquito bites and cleaning and disinfecting after being bitten by mosquitoes

WARNINGS

*For extemal use only.
*Flammable. keep away from fire or flame.

Do not use " with electrocautery procedures " in the eyes. lf contact occurs, flush eyes with water.

When using this product keep out of eyes, ears, and mouth. In case of contact with eyes, rinse eyes thoroughly with water.

*Stop use if irritation and redness develop. If condition persists consult your health care practioner.

*Stop use and ask a doctor if irritation or rash occurs. These may be signs of a serious condition.

Keep out of reach of children. If swallowed, get medical help or contact a Poison Control Center right away.

DOSAGE AND ADMINISTRATION

Mainly used for wiping before mosquito bites and cleaning and disinfecting after being bitten by mosquitoes.One piece at a time.

STORAGE AND HANDLING

Store at room temperature

INACTIVE INGREDIENT

water